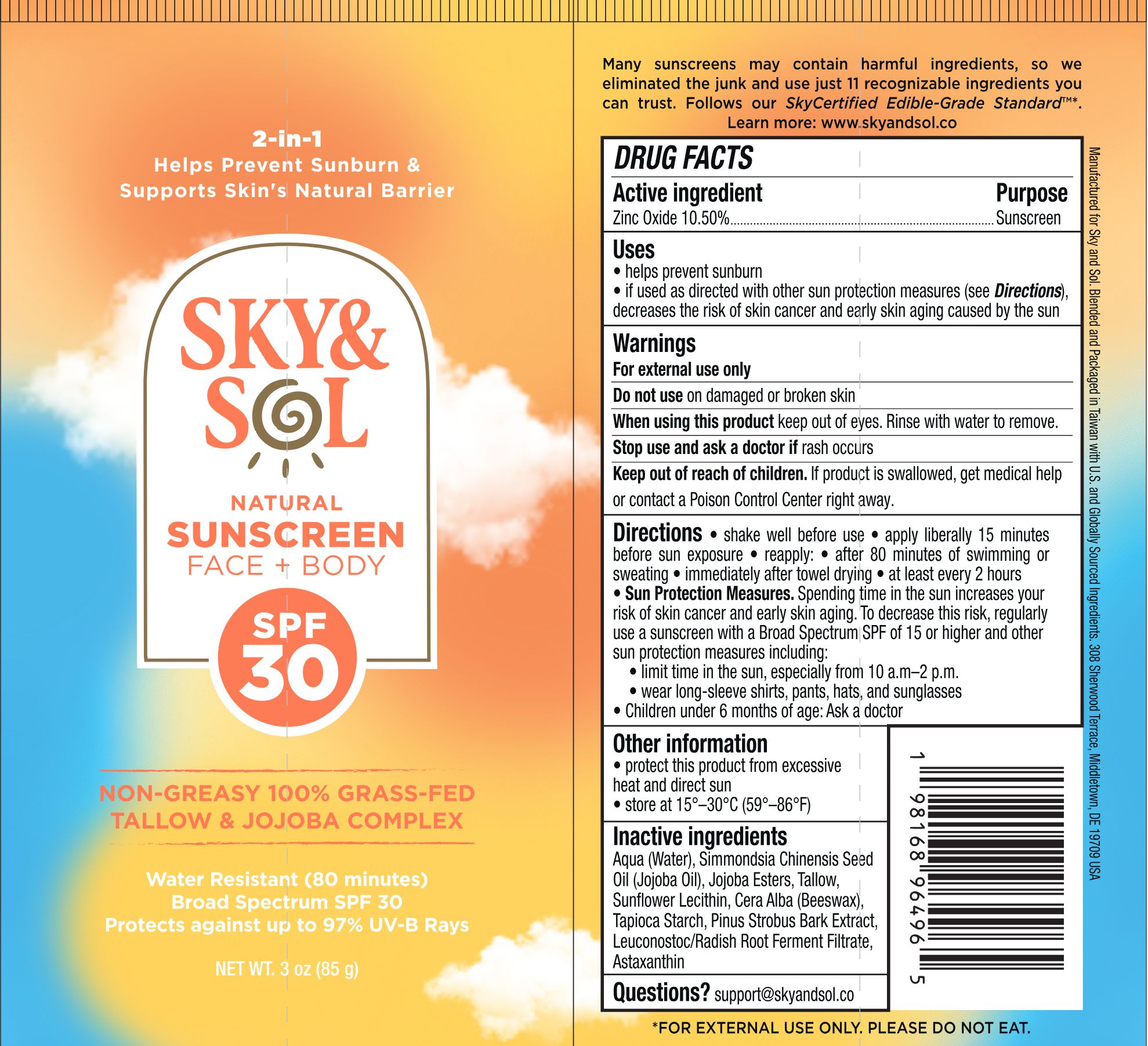 DRUG LABEL: Sky and Sol Face and Body Sunscreen Spf 30
NDC: 84632-3032 | Form: CREAM
Manufacturer: Delta Ecommerce LLC
Category: otc | Type: HUMAN OTC DRUG LABEL
Date: 20260121

ACTIVE INGREDIENTS: ZINC OXIDE 8.93 g/85 g
INACTIVE INGREDIENTS: SIMMONDSIA CHINENSIS (JOJOBA) SEED OIL; BEESWAX; PINUS STROBUS BARK; ASTAXANTHIN; AQUA; TALLOW; HYDROLYZED JOJOBA ESTERS; LEUCONOSTOC/RADISH ROOT FERMENT FILTRATE; LECITHIN, SUNFLOWER; TAPIOCA STARCH

PURPOSE

Sunscreen

INDICATIONS AND USAGE

helps prevent sunburn; if used as directed with other sun protection measures (see Directions), decreases the risk of skin cancer and early skin aging caused by the sun

DOSAGE AND ADMINISTRATION

Shake well befoe use.
Apply literally 15 minutes before sun exposure.
Reapply:
after 80 minutes of swimming or sweating
immediately after towel drying
at least every 2 hours

WARNINGS

For external use only.
Do not use on damaged or broken skin.
Stop use and ask a doctor if rash occurs.
When using this product, keep out of eyes. Rinse with water to remove.

KEEP OUT OF REACH OF CHILDREN

Keep out of reach of childen. If swallowed, get medical help or contact a Poison Control Center right away.

INACTIVE INGREDIENT

AQUA
TALLOW
ZINC OXIDE
JOJOBA OIL
HYDROLYZED JOJOBA ESTERS
LECITHIN, SUNFLOWER
BEESWAX
LIMONIA ACIDISSIMA BARK
BABASSU OIL
ASTAXANTHIN
LEUCONOSTOC/RADISH ROOT FERMENT FILTRATE